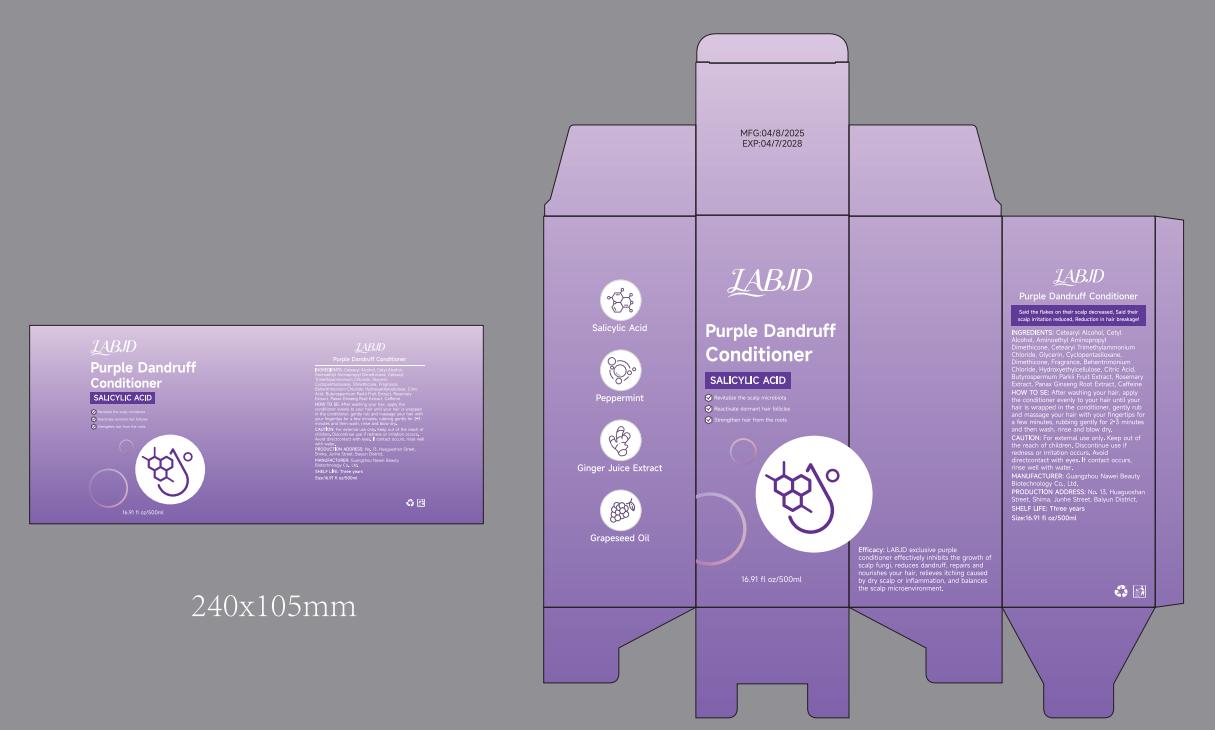 DRUG LABEL: Purple Dandruff Conditioner
NDC: 85605-456 | Form: LIQUID
Manufacturer: Guangzhou Nawei Beauty Biotechnology Co., Ltd
Category: homeopathic | Type: HUMAN OTC DRUG LABEL
Date: 20250430

ACTIVE INGREDIENTS: CETEARYL ALCOHOL 16 g/500 1
INACTIVE INGREDIENTS: CETYL HYDROXYETHYLCELLULOSE (550000 MW); BEHENTRIMONIUM CHLORIDE; CITRIC ACID; CETYL ALCOHOL; GLYCERIN; CYCLOPENTASILOXANE; CETEARTRIMONIUM CHLORIDE; FRAGRANCE GREEN APPLE ORC2001072; DIMETHICONOL (40 CST); CAFFEINE

ACTIVE INGREDIENT

CETEARYL ALCOHOL

PURPOSE

exclusive purple conditioner effectively inhibits the growth of scalp fungi

Keep out of the reach of children

INDICATIONS AND USAGE

After washing your hair,apply the conditioner evenly to your hair until your hair is wrapped in the conditioner,

WARNINGS

CAUTION:For external use only

DOSAGE AND ADMINISTRATION

Size:16.91 fl oz/500ml

INACTIVE INGREDIENT

CETYL ALCOHOL,AMINOETHYLAMINOPROPYL DIMETHICONE,
CETEARTRIMONIUM CHLORIDE,GLYCERIN,CYCLOPENTASILOXANE,
DIMETHICONOL,FRAGRANCE,BEHENTRIMONIUM CHLORIDE,
HYDROXYETHYLCELLULOSE,CITRIC ACID,UTYROSPERMUM PARKII(SHEA)FRUIT EXTRACT,
ROSMARINUS OFFICINALIS ROSEMARY) EXTRACT,PANAX GINSENG ROOT EXTRACT,
CAFFEINE